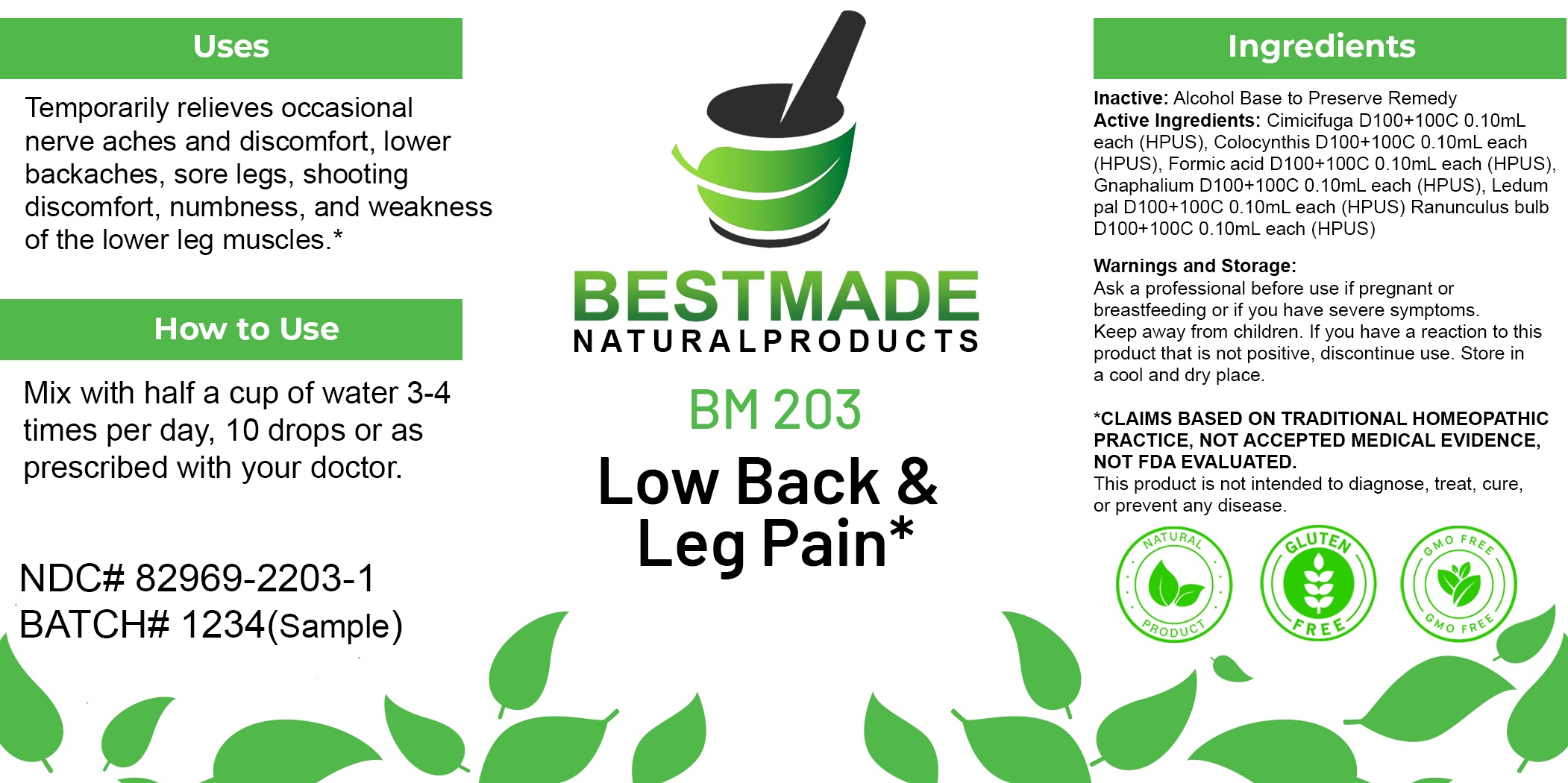 DRUG LABEL: Bestmade Natural Products BM203
NDC: 82969-2203 | Form: LIQUID
Manufacturer: Bestmade Natural Products
Category: homeopathic | Type: HUMAN OTC DRUG LABEL
Date: 20250225

ACTIVE INGREDIENTS: PSEUDOGNAPHALIUM OBTUSIFOLIUM WHOLE 30 [hp_C]/30 [hp_C]; FORMIC ACID 30 [hp_C]/30 [hp_C]; RANUNCULUS BULBOSUS WHOLE 30 [hp_C]/30 [hp_C]; BLACK COHOSH 30 [hp_C]/30 [hp_C]; RHODODENDRON TOMENTOSUM LEAFY TWIG 30 [hp_C]/30 [hp_C]; CITRULLUS COLOCYNTHIS FRUIT PULP 30 [hp_C]/30 [hp_C]
INACTIVE INGREDIENTS: ALCOHOL 30 [hp_C]/30 [hp_C]

BM203

DOSAGE AND ADMINISTRATION

How to Use

Mix with half a cup of water 3-4 times per day. Ages 12 or older, 10 drops. Ages 12-2, 5 drops. Ages 2 and under, consult your Doctor.

Inactive:

Alcohol Base to Preserve Product

ACTIVE INGREDIENTS

Cimicifuga D100+100C 0.10mL each (HPUS), Colocynthis D100+100C 0.10mL each (HPUS), Formic acid D100+100C 0.10mL each (HPUS), Gnaphalium D100+100C 0.10mL each (HPUS), Ledum pal D100+100C 0.10mL each (HPUS) Ranunculus bulb D100+100C 0.10mL each (HPUS)

KEEP OUT OF REACH OF CHILDREN

Warnings and Storage:

Ask a professional before use if pregnant or breastfeeding or if you have severe symptoms.

Keep away from children. If you have a reaction to this product that is not positive, discontinue use. Store in a cool and dry place

*CLAIMS BASED ON TRADITIONAL HOMEOPATHIC PRACTICE, NOT ACCEPTED MEDICAL EVIDENCE NOT FDA EVALUATED.
This product is not intended to diagnose, treat, cure, or prevent any disease.

Warnings and Storage:

Ask a professional before use if pregnant or breastfeeding or if you have severe symptoms.

Keep away from children. If you have a reaction to this product that is not positive, discontinue use. Store in a cool and dry place

*CLAIMS BASED ON TRADITIONAL HOMEOPATHIC PRACTICE, NOT ACCEPTED MEDICAL EVIDENCE NOT FDA EVALUATED.
This product is not intended to diagnose, treat, cure, or prevent any disease.

Uses
Temporarily relieves occasional nerve aches and discomfort, lower backaches, sore legs, shooting discomfort, numbness, and weakness of the lower leg muscles.*

Uses
Temporarily relieves occasional nerve aches and discomfort, lower backaches, sore legs, shooting discomfort, numbness, and weakness of the lower leg muscles.*

Entire package label